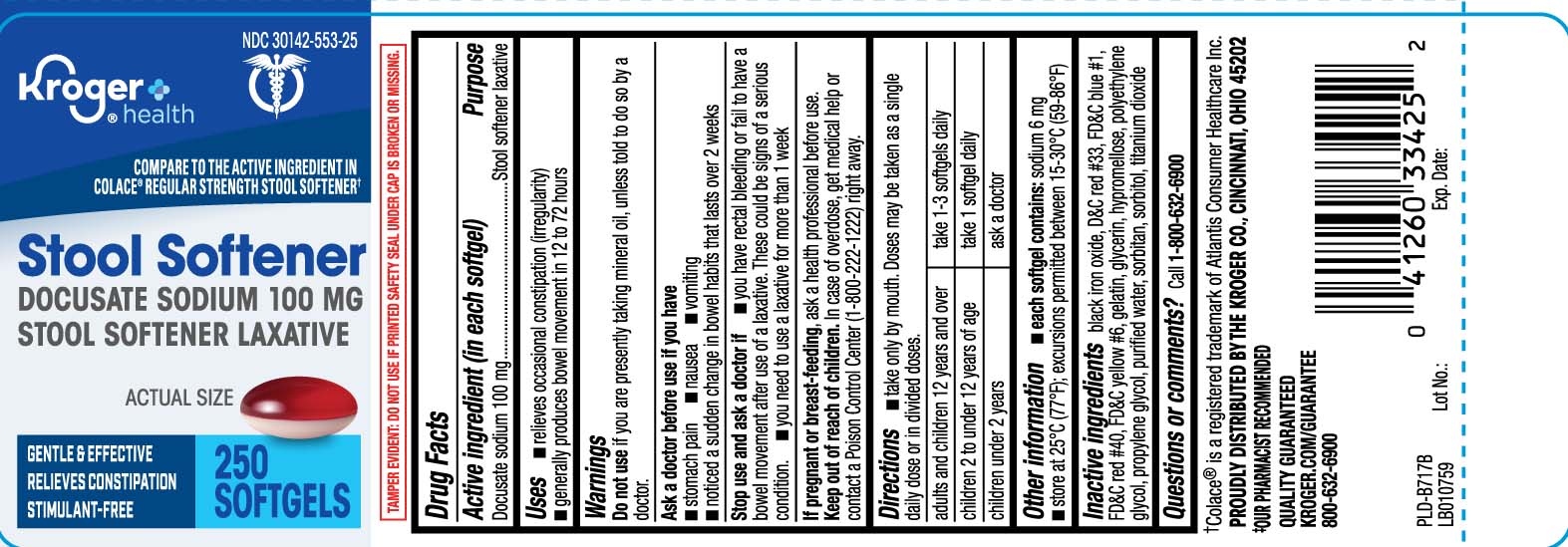 DRUG LABEL: Stool Softener Laxative
NDC: 30142-553 | Form: CAPSULE, LIQUID FILLED
Manufacturer: The Kroger Co.
Category: otc | Type: HUMAN OTC DRUG LABEL
Date: 20260213

ACTIVE INGREDIENTS: DOCUSATE SODIUM 100 mg/1 1
INACTIVE INGREDIENTS: D&C RED NO. 33; FD&C BLUE NO. 1; FD&C RED NO. 40; FD&C YELLOW NO. 6; GELATIN; GLYCERIN; POLYETHYLENE GLYCOL, UNSPECIFIED; PROPYLENE GLYCOL; WATER; SORBITAN; SORBITOL; TITANIUM DIOXIDE; HYPROMELLOSE, UNSPECIFIED; FERROSOFERRIC OXIDE

Drug Facts

Active ingredient (in each softgel)

Docusate sodium 100 mg

Purpose

Stool softener laxative

Uses

- relieves occasional constipation (irregularity)
- generally produces bowel movement in 12 to 72 hours

Warnings

Do not use

if you are presently taking mineral oil, unless told to do so by a doctor.

Ask a doctor before use if you have

- stomach pain
- nausea
- vomiting
- a sudden change in bowel habits that lasts over 2 weeks

Stop use and ask a doctor if

- you have rectal bleeding or fail to have a bowel movement after use of a laxative. These could be signs of a serious condition.
- you need to use a laxative for more than 1 week

If pregnant or breast-feeding,

ask a health professional before use.

Keep out of reach of children.

In case of overdose, get medical help or contact a Poison Control Center (1-800-222-1222) right away.

Directions

- take only by mouth. Doses may be taken as a single daily dose or in divided doses.

adults and children 12 years and over | take 1-3 softgels daily .
children 2 to under 12 years of age | take 1 softgel daily
children under 2 years of age | ask a doctor

Other information

- each softgel contains:sodium 6 mg
- store at 25ºC (77ºF); excursions permitted between 15-30ºC (59-86ºF)

Inactive ingredients

black iron oxide, D&C red #33, FD&C blue #1, FD&C red #40, FD&C yellow #6, gelatin, glycerin, hypromellose, polyethylene glycol, propylene glycol, purified water, sorbitan, sorbitol, titanium dioxide

Questions or comments?

1-800-632-6900

Principal Display Panel

COMPARE TO THE ACTIVE INGREDIENT IN COLACE® REGULAR STRENGTH STOOL SOFTENER†

Stool Softener

DOCUSATE SODIUM 100 mg

STOOL SOFTENER LAXATIVE

Gentle & EFFECTIVE

RELIEVES CONSTIPATION

STIMULANT-FREE

SOFTGELS

†Colace® is a registered trademark of Atlantis Consumer Healthcare Inc.

TAMPER EVIDENT: DO NOT USE IF PRINTED SAFETY SEAL UNDER CAP IS BROKEN OR MISSING

DISTRIBUTED BY THE KROGER CO., CINCINNATI, OHIO 45202

www.kroger.com

Product Label

KROGER Stool Softener